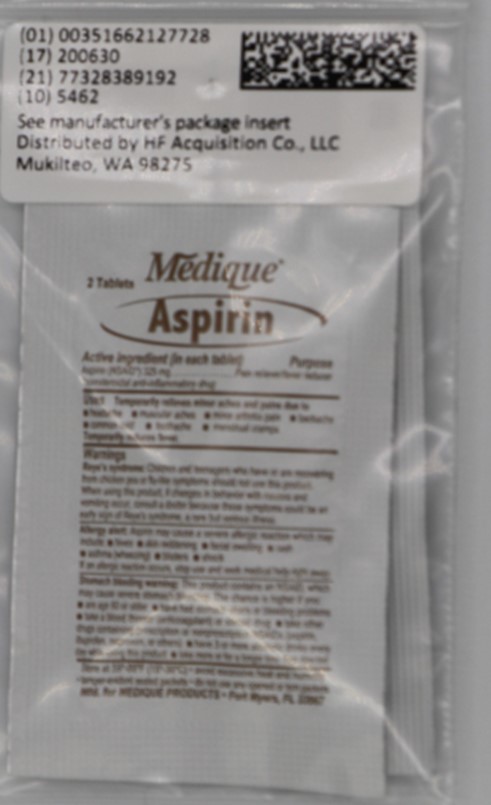 DRUG LABEL: MEDIQUE ASPIRN
NDC: 51662-1277 | Form: TABLET, FILM COATED
Manufacturer: HF Acquisition Co LLC, DBA HealthFirst
Category: otc | Type: HUMAN OTC DRUG LABEL
Date: 20241119

ACTIVE INGREDIENTS: ASPIRIN 325 mg/1 1
INACTIVE INGREDIENTS: CROSCARMELLOSE SODIUM; HYPROMELLOSES; STARCH, CORN; CELLULOSE, MICROCRYSTALLINE; TITANIUM DIOXIDE; MINERAL OIL

ACTIVE INGREDIENT

Aspirin (NSAID*) 325mg *nonsteroidal anti-inflammatory drug

PURPOSE

Pain Reliever/Fever Reducer

WHEN USING

Reye's Syndrome: Children and teenagers who have or are recovering from chicken pox or Flu-like symptoms should not use this product. When using this product, if changes in behavior with nausea and vomiting occur, consult a doctor because these symptoms could be an early sign of Reye's syndrome, a rare but serious illness.

Allergy Alert: Aspirin may cause a severe allergic reaction which may include: hives, skin reddening, facial swelling, rash, asthma (wheezing), blisters or shock. If an allergic reaction occurs, stop use and seek medical help right away.

Stomach bleeding warning: this contains an NSAID, which may cause severe stomach bleeding. The chance is higher if you: are age 60 or older; have had stomach ulcers or bleeding problems, take a blood thinner (anticoagulant) or steroid drug; take other drugs containing prescription or nonprescription NSAIDs (aspirin, ibuprofen, naproxen or others), have 3 or more alcoholic drinks everyday while using this problem, take more for a longer time than directed.

Do not use if you have ever had an allergic reaction to any other pain reliever/fever reducer; right before or after heart surgery, if you are taking a prescription drug for gout, diabetes or arthritis.

Ask a doctor before use if: stomach bleeding warning applies to you, you have a history of stomach problems such as heartburn, you have high blood pressure, heart disease, liver cirrhosis or kidney disease, you are taking a diuretic.

Ask a Doctor or Pharmacist before use if you are: under a doctor's care for any serious condition, taking any other drug.

When using this product: take with food or milk if stomach upset occurs

Stop use and Ask a Doctor if: you experience any of the following signs of stomach bleeding, you feel faint, vomit blood, have bloody or black stools, have stomach pain that does not get better, gets worse or lasts more than 10 days, fever gets worse or lasts more than 3 days, you have difficulty swallowing, if ringing in the ears or loss of hearing occurs, redness or swelling is present in painful areas, or any new symptoms appear.

If pregnant or Breastfeeding, ask a health professional before use. It is especially important not to use aspirin during the last 3 months of pregnancy unless directed to do so by a doctor because it may cause problems in the unborn child or complications during deliver.

Keep out of reach of Children. In case of overdose, get medical help or contact a poison control center right away.

DIRECTIONS

Do not use more than directed - the smallest effective dosage should be used. Drink a full glass of water with each dose. Do not take longer than 10 days, unless directed by a doctor.

Adults and Children (12 years and older): take 1 or 2 tablets with water every 4 hours as needed. Do not take more than 12 tablets in 24 hours or as directed as a doctor.

Children under 12 years: Do not give to children under 12 years of age

Avoid excessive heat and humidity, do not use any open or torn packets.

USE

Temporarily relieves minor aches and pains associated with: headache, muscular aches, minor arthritis pain, backache, common cold, toothache, menstrual cramps, temporarily reduces fever.

Ask a doctor before use if: stomach bleeding warning applies to you, you have a history of stomach problems such as heartburn, you have high blood pressure, heart disease, liver cirrhosis or kidney disease, you are taking a diuretic.

Ask a Doctor or Pharmacist before use if you are: under a doctor's care for any serious condition, taking any other drug.

Stop use and Ask a Doctor if: you experience any of the following signs of stomach bleeding, you feel faint, vomit blood, have bloody or black stools, have stomach pain that does not get better, gets worse or lasts more than 10 days, fever gets worse or lasts more than 3 days, you have difficulty swallowing, if ringing in the ears or loss of hearing occurs, redness or swelling is present in painful areas, or any new symptoms appear.

PREGNANCY OR BREAST FEEDING

If pregnant or Breastfeeding, ask a health professional before use. It is especially important not to use aspirin during the last 3 months of pregnancy unless directed to do so by a doctor because it may cause problems in the unborn child or complications during deliver.

Keep out of reach of Children. In case of overdose, get medical help or contact a poison control center right away.

Do not use if you have ever had an allergic reaction to any other pain reliever/fever reducer; right before or after heart surgery, if you are taking a prescription drug for gout, diabetes or arthritis.

HOW SUPPLIED

1 (2 Pack) 325 MG Packet

DOSAGE AND ADMINISTRATION

Adults and Children (12 years and older): take 1 or 2 tablets with water every 4 hours as needed. Do not take more than 12 tablets in 24 hours or as directed as a doctor.

INDICATIONS AND USAGE

Pain Reliever/Fever Reducer

Reye's Syndrome: Children and teenagers who have or are recovering from chicken pox or Flu-like symptoms should not use this product. When using this product, if changes in behavior with nausea and vomiting occur, consult a doctor because these symptoms could be an early sign of Reye's syndrome, a rare but serious illness.

Allergy Alert: Aspirin may cause a severe allergic reaction which may include: hives, skin reddening, facial swelling, rash, asthma (wheezing), blisters or shock. If an allergic reaction occurs, stop use and seek medical help right away.

Stomach bleeding warning: this contains an NSAID, which may cause severe stomach bleeding. The chance is higher if you: are age 60 or older; have had stomach ulcers or bleeding problems, take a blood thinner (anticoagulant) or steroid drug; take other drugs containing prescription or nonprescription NSAIDs (aspirin, ibuprofen, naproxen or others), have 3 or more alcoholic drinks everyday while using this problem, take more for a longer time than directed.

Do not use if you have ever had an allergic reaction to any other pain reliever/fever reducer; right before or after heart surgery, if you are taking a prescription drug for gout, diabetes or arthritis.

Ask a doctor before use if: stomach bleeding warning applies to you, you have a history of stomach problems such as heartburn, you have high blood pressure, heart disease, liver cirrhosis or kidney disease, you are taking a diuretic.

Ask a Doctor or Pharmacist before use if you are: under a doctor's care for any serious condition, taking any other drug.

When using this product: take with food or milk if stomach upset occurs

Stop use and Ask a Doctor if: you experience any of the following signs of stomach bleeding, you feel faint, vomit blood, have bloody or black stools, have stomach pain that does not get better, gets worse or lasts more than 10 days, fever gets worse or lasts more than 3 days, you have difficulty swallowing, if ringing in the ears or loss of hearing occurs, redness or swelling is present in painful areas, or any new symptoms appear.

If pregnant or Breastfeeding, ask a health professional before use. It is especially important not to use aspirin during the last 3 months of pregnancy unless directed to do so by a doctor because it may cause problems in the unborn child or complications during deliver.

Keep out of reach of Children. In case of overdose, get medical help or contact a poison control center right away.

Do not use more than directed - the smallest effective dosage should be used. Drink a full glass of water with each dose. Do not take longer than 10 days, unless directed by a doctor.

INACTIVE INGREDIENT

CELLULOSE, MICROCRYSTALLINE (UNII: OP1R32D61U)
CROSCARMELLOSE SODIUM (UNII: M28OL1HH48)
TITANIUM DIOXIDE (UNII: 15FIX9V2JP)
MINERAL OIL (UNII: T5L8T28FGP)
HYPROMELLOSES (UNII: 3NXW29V3WO)
STARCH, CORN (UNII: O8232NY3SJ)